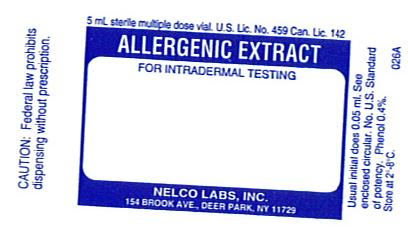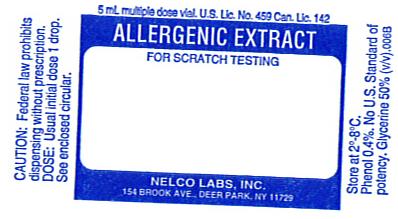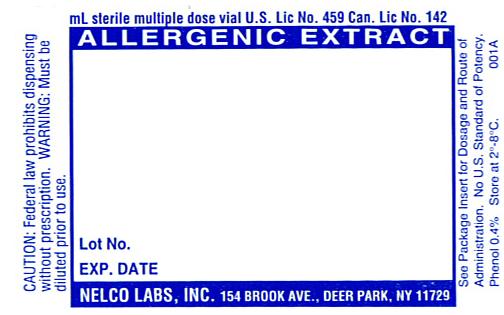 DRUG LABEL: Short Ragweed Pollen
NDC: 36987-3384 | Form: INJECTION, SOLUTION
Manufacturer: Nelco Laboratories, Inc.
Category: prescription | Type: HUMAN PRESCRIPTION DRUG LABEL
Date: 20091207

ACTIVE INGREDIENTS: AMBROSIA ARTEMISIIFOLIA POLLEN 20000 [PNU]/1 mL
INACTIVE INGREDIENTS: SODIUM CHLORIDE; SODIUM BICARBONATE; PHENOL; WATER; GLYCERIN

Allergenic Extract

WARNING

Diagnostic and therapeutic allergenic extracts are intended to be administered by a physician who is an allergy specialist and experienced in allergenic diagnostic testing and immunotherapy and the emergency care of anaphylaxis.

This product should not be injected intravenously. Deep subcutaneous routes have been safe. Sensitive patients may experience severe anaphylactic reactions resulting in respiratory obstruction, shock, coma and/or death. (See Adverse Reactions)

Serious adverse reactions should be reported to Nelco Laboratories immediately and a report filed to: MedWatch, The FDA Medical Product Problem Reporting Program, at 5600 Fishers Lane, Rockville, Md. 20852-9787, call 1-800-FDA-1088.

Extreme caution should be taken when using allergenic extracts for patients who are taking beta-blocker medications. In the event of a serious adverse reaction associated with the use of allergenic extracts, patients receiving beta-blockers may not be responsive to epinephrine or inhaled brochodialators.(1) (See Precautions)

Allergenic extracts should be used with caution for patients with unstable or steroid-dependent asthma or underlying cardiovascular disease. (See Contraindications)

DESCRIPTION

Allergenic extracts are sterile solutions consisting of the extractable components from various biological sources including pollens, inhalants, molds, animal epidermals and insects. Aqueous extracts are prepared using cocas fluid containing NaCl 0.5%, NaHCO3 0.0275%, WFI, preservative 0.4% Phenol. Glycerinated allergenic extracts are prepared with cocas fluid and glycerin to produce a 50% (v/v) allergenic extract. Allergenic Extracts are supplied as concentrations designated as protein nitrogen units (PNU) or weight/volume (w/v) ratio. Standardized extracts are designated in Bioequivalent Allergy Units (BAU) or Allergy Units (AU). (See product insert for standardized extracts)

For diagnostic purposes, allergenic extracts are to be administered by prick-puncture or intradermal routes. Allergenic extracts are administered subcutaneously for immunotherapy injections.

CLINICAL PHARMACOLOGY

The pharmacological action of allergenic extracts used diagnostically is based on the liberation of histamine and other substances when the allergen reacts with IgE antibodies attached to the mast cells. When allergenic extracts are used for immunotherapy, the effect is an increase in immunoglobulin G (IgG) and an increased T suppresser lymphocyte which interferes with the allergic response.(2) With repeated administration of allergenic extracts changes develop in regards to IgG and IgE production and mediator-releasing cells. The histamine release response is reduced in some patients.

INDICATIONS AND USAGE

Allergenic extracts are indicated for use in diagnostic testing and as part of a treatment regime for allergic disease, as established by allergy history and skin test reactivity.

Allergenic extracts are indicated for the treatment of allergen specific allergic disease for use as hyposensitization or immunotherapy when avoidance of specific allergens can not be attained. The use of allergenic extracts for therapeutic purpose has been established by well-controlled clinical studies. Allergenic extracts may be used as adjunctive therapy along with pharmacotherapy which includes antihistamines, corticosteroids, and cromoglycate, and avoidance measures. Allergenic extracts for therapeutic use should be given using only the allergen selection to which the patient is allergic, has a history of exposure and are likely to be exposed to again.

CONTRAINDICATIONS

Allergenic extracts should not be used if the patient has asthma, cardiovascular disease, emphysema, diabetes, bleeding diathesis or pregnancy, unless a specific diagnosis of type 1 allergic disease is made based on skin testing and the benefits of treatment outweigh the risks of an adverse reaction during testing or treatment. Allergenic extracts are not indicated for use in patients who are not clinically allergic or who are not skin reactive to an allergen. Allergenic extracts should be discontinued or the concentration of potency substantially reduced in patients who experience unacceptable adverse reactions.

WARNINGS

DO NOT INJECT INTRAVENOUSLY.

Epinephrine 1:1000 should be available.

Concentrated extracts must be diluted with sterile diluent prior to first use on a patient for treatment or intradermal testing. All concentrates of glycerinated allergenic extracts have the ability to cause serious local and systemic reactions including death in sensitive patients. Sensitive patients may experience severe anaphylactic reactions resulting in respiratory obstruction, shock, coma and /or death.(4) (See Adverse Reactions) An allergenic extract should be temporarily withheld from patients or the dose of the extract adjusted downward if any of the following conditions exist: (1) Severe symptoms of rhinitis and/or asthma (2) Infections or flu accompanied by fever and (3) Exposure to excessive amounts of clinically relevant allergen prior to a scheduled injection. When switching patients to a new lot of the same extract the initial dose should be reduced 3/4 so that 25% of previous dose is administered.

PRECAUTIONS

GENERAL: Epinephrine 1:1000 should be available as well as personnel trained in administering emergency treatment. Allergenic Extracts are not intended for intravenous injections. For safe and effective use of allergenic extracts, sterile diluents, sterile vials, sterile syringes should be used and aseptic precautions observed when making a dilution and/or administering the allergenic extract injection. A sterile tuberculin syringe graduated in 0.1 ml units to measure each dose for the prescribed dilution should be used. To reduce the risk of an occurrence of adverse reactions, begin with a careful personal history plus a physical exam. Confirm your findings with scratch or intradermal skin testing.

Standardized extracts are those labeled in AU/ml units or BAU/ml units. Standardized extracts are not interchangeable with extracts previously labeled as wt/vol or PNU/ml. Before administering a standardized extract, read the accompanying insert contained with standardized extracts.

Information for Patients: All concentrates of allergenic extracts have the ability to cause serious local and systemic reactions including death in sensitive patients. Patients should be informed of this risk prior to skin testing and immunotherapy. Patients should be instructed to recognize adverse reaction symptoms that may occur and to report all adverse reactions to a physician. Patients should be instructed to remain in the office for 30 minutes during testing using allergenic extracts and at least 30 minutes after therapeutic injections using allergenic extracts.

DRUG INTERACTIONS: Some drugs may affect the reactivity of the skin; patients should be instructed to avoid medications, particularly antihistamines and sympathomimetic drugs, for at least 24 hours prior to skin testing. Antihistamines and Hydroxyzine can significantly inhibit the immediate skin test reactions as they tend to neutralize or antagonize the action of histamine.(3) This effect has been primarily documented when testing was performed within 1 to 2 hours after drug ingestion. Partial inhibition of the skin test reaction had been observed for longer periods. Epinephrine injection inhibits the immediate skin test reactions for several hours. Patients on delayed absorption antihistamine tablets should be free of such medication for 48 hours before testing. Patients using Astemizole (Hismanal) may experience prolonged suppression and should be free from such medication for up to 6 to 8 weeks prior to testing. Refer to package insert from an applicable long acting antihistamine manufacturer for additional information.

Extreme caution should be taken when using allergenic extracts on patients who are taking beta-blockers. Patients on non-selective beta blockers may be more reactive to allergens given for testing or treatment and may be unresponsive to the usual doses of epinephrine used to treat allergic reactions.

Carcinogenesis, mutagenesis, impairment of fertility:

Long term studies in animals have not been conducted with allergenic extracts to determine their potential carcinogenicity, mutagenicity or impairment of fertility.

Pregnancy: Category C: Animal reproduction studies have not been conducted with Allergenic Extracts. It is not known whether allergenic extracts can cause fetal harm when administered to pregnant women or can affect reproduction capacity. Allergenic extracts should be given to pregnant women only if clearly needed.

Nursing Mothers: It is not known whether this drug appears in human milk. Because many drugs are detected in human milk, caution should be exercised when Allergenic Extracts are administered to a nursing woman. There are no current studies on extract components in human milk, or their effect on the nursing infant.

Pediatric Use: Allergenic extracts have been used in children over two years of age.(5)

ADVERSE REACTIONS

Adverse systemic reactions usually occur within minutes and consist primarily of allergic symptoms such as: generalized skin erythema, urticaria, pruritus, angioedema, rhinitis, wheezing, laryngeal edema, itching of nose and throat, breathlessness, dyspnea, coughing, hypotension and marked perspiration. Less commonly, nausea, emesis, abdominal cramps, diarrhea and uterine contractions may occur. Severe reactions may cause anaphylaxis or shock and loss of consciousness and rarely death.

The treatment of systemic allergic reactions is dependent upon the system complex. Antihistamines may offer relief of recurrent urticaria, associated skin reactions and gastrointestinal symptoms. Corticosteroids may provide benefit if symptoms are prolonged or recurrent. (See Overdose section)

Local Reactions consisting of erythema, itching, swelling tenderness and sometimes pain may occur at the injection site. These reactions may appear within a few minutes to hours and persist for several days. Local cold applications and oral antihistamines may be effective treatment. For marked and prolonged local reactions the use of antihistamines or anti-inflammatory medications may be dictated. Serious adverse reactions should be reported to Nelco Laboratories immediately and a report can be filed to: MedWatch, The FDA Medical Product Problem Reporting Program, at 5600 Fishers Lane, Rockville, MD 20852-9787, call 1-800-FDA-1088.

OVERDOSAGE

Overdose can cause both local and systemic reactions. An overdose may be prevented by careful observation and questioning of the patient about the previous injection.

If systemic or anaphylactic reaction, does occur, apply a tourniquet above the site of injection and inject intramuscularly or subcutaneously 0.3 to 0.5ml of 1:1000 Epinephrine Hydrochloride into the opposite arm. The dose may be repeated in 5-10 minutes if necessary. Loosen the tourniquet at least every 10 minutes. The Epinephrine Hydrochloride 1:1000 dose for infants to 2 years is 0.05 to 0.1 ml, for children 2 to 6 years it is 0.15 ml, for children 6-12 years it is 0.2 ml.

Patients unresponsive to Epinephrine may be treated with Theophylline. Studies on asthmatic subjects reveal that plasma concentrations of Theophylline of 5 to 20 µg/ml are associated with therapeutic effects. Toxicity is particularly apparent at concentrations greater than 20 µg/ml. A loading dose of Aminophylline of 5.8 mg/kg intravenously followed by 0.9 mg/kg per hour results in plasma concentrations of approximately 10 µg/ml for patients not previously receiving theophylline. (Mitenko and Ogilive, Nicholoson and Chick,1973)

Other beta-adrenergic drugs such as Isoproterenol, Isoetharine, or Albuterol may be used by inhalation. The usual dose to relieve broncho-constriction in asthma is 0.5 ml of the 0.5% solution for Isoproterenol HCl. The Albuterol inhaler delivers approximately 90 mcg of Albuterol from the mouthpiece. The usual dosage for adults and children would be two inhalations repeated every 4-6 hours. Isoetharine supplied in the Bronkometer unit delivers approximately 340 mcg Isoetharine. The average dose is one to two inhalations. Respiratory obstruction not responding to parenteral or inhaled bronchodilators may require oxygen, intubation and the use of life support systems.

DOSAGE AND ADMINISTRATION

General Precautions

Parenteral drug products should be inspected visually for particulate matter and discoloration prior to administration whenever solution and container permits.

The dosage of allergenic extracts is dependent upon the purpose of the administration. Allergenic extracts can be administered for diagnostic use or for therapeutic use.

When allergenic extracts are administered for diagnostic use, the dosage is dependent upon the method used. Two methods commonly used are scratch testing and intradermal testing. Both types of tests result in a wheal and flare response at the site of the test which usually develops rapidly and may be read in 20-30 minutes.

Diagnostic Use: Scratch Testing Method

Scratch testing is considered a simple and safe method although less sensitive than the intradermal test. Scratch testing can be used to determine the degree of sensitivity to a suspected allergen before using the intradermal test. This combination lessens the severity of response to an allergen which can occur in a very sensitive patient.

The most satisfactory testing site is the patient's back or volar surface of the arms from the axilla to 2.5 or 5cm above the wrist, skipping the anti-cubital space. If using the back as a testing site, the most satisfactory area are from the posterior axillary fold to 2.5 cm from the spinal column, and from the top of the scapula to the lower rib margins.

Allergenic extracts for diagnostic use are to be administered in the following manner: To scratch surface of skin, use a circular scarifier. Do not draw blood. Tests sites should be 4 cm apart to allow for wheal and flare reaction. 1-30 scratch tests may be done at a time. A separate sterile scratch instrument is to be used on each patient to prevent transmission of homologous serum hepatitis or other infectious agents from one patient to another.

The recommended usual dosage for Scratch testing is one drop of allergen applied to each scratch site. Do not let dropper touch skin. Always apply a control scratch with each test set. Sterile Diluent (for a negative control) is used in exactly the same way as an active test extract. Histamine may be used as a positive control. Scratch or prick test sites should be examined at 15 and 30 minutes. To prevent excessive absorption, wipe off antigens producing large reactions as soon as the wheal appears. Record the size of the reaction.

Interpretation of Scratch Test

Skin tests are graded in terms of the wheal and erythema response noted at 10 to 20 minutes. Wheal and erythema size may be recorded by actual measurement as compared with positive and negative controls. A positive reaction consists of an area of erythema surrounding the scarification that is larger than the control site. For uniformity in reporting reactions, the following system is recommended. (6)

REACTION | SYMBOL | CRITERIA
Negative | - | No wheal. Erythema absent or very slight (not more than 1 mm diameter).
One Plus | + | Wheal absent or very slight erythema present (not more than 3 mm diameter).
Two Plus | ++ | Wheal not more than 3mm or erythema not more than 5mm diameter.
Three Plus | +++ | Wheal between 3mm and 5mm diameter, with erythema. Possible pseudopodia and itching.
Four Plus | ++++ | A larger reaction with itching and pain.

Diagnostic Use: Intradermal Skin Testing Method

Do not perform intradermal test with allergens which have evoked a 2+ or greater response to a Scratch test. Clean test area with alcohol, place sites 5 cm apart using separate sterile tuberculin syringe and a 25 gauge needle for each allergen. Insert needle tip, bevel up, into intracutaneous space. Avoid injecting into blood vessel, pull back gently on syringe plunger, if blood enters syringe change position of needle. The recommended dosage and range for intradermal testing is 0.05 ml of not more than 100 pnu/ml or 1:1000 w/v (only if puncture test is negative) of allergenic extract. Inject slowly until a small bleb is raised. It is important to make each bleb the same size.

Interpretation of Intradermal Test:

The patient's reaction is graded on the basis of size of wheal and flare as compared to control. Use 0.05 ml sterile diluent as a negative control to give accurate interpretation. The tests may be accurately interpreted only when the saline control site has shown a negative response. Observe patient for at least 30 minutes. Tests can be read in 15-20 minutes. Edema, erythema and presence of pseudopods, pain and itching may be observed in 4 plus reactions. For uniformity in reporting reactions the following system is recommended. (6)

REACTION | SYMBOL | CRITERIA
Negative | - | No increase in size of bleb since injection. No erythema.
One Plus | + | An increase in size of bleb to a wheal not more than 5mm diameter, with associated erythema.
Two Plus | ++ | Wheal between 5mm and 8mm diameter with erythema.
Three Plus | +++ | Wheal between 8mm and 12mm diameter with erythema and possible pseudopodia and itching or pain.
Four Plus | ++++ | Any larger reaction with itch and pain, and possible diffuse blush of the skin surrounding the reaction area.

Therapeutic Use: Recommended dosage & range

Check the listed ingredients to verify that it matches the prescription ordered. When using a prescription set, verify the patient's name and the ingredients listed with the prescription order. Assess the patient's physical and emotional status prior to giving as injection. Do not give injections to patients who are in acute distress. Parenteral drug products should be inspected visually for particulate matter and discoloration prior to administration, whenever solution and container permit.

Dosage of allergenic extracts is a highly individualized matter and varies according to the degree of sensitivity of the patient, his clinical response and tolerance to the extract administered during the early phases of an injection regimen. The dosage must be reduced when transferring a patient from non-standardized or modified extract to standardized extract. Any evidence of a local or generalized reaction requires a reduction in dosage during the initial stages of immunotherapy as well as during maintenance therapy. After therapeutic injections patients should be observed for at least 20 minutes for reaction symptoms.

SUGGESTED DOSAGE SCHEDULE

The following schedule may act as a guide. This schedule has not been proven to be safe or effective. Sensitive patients may begin with smaller doses of weaker solutions and the dosage increments can be less.

STRENGTH | DOSE | VOLUME
Vial #1 | 1 | 0.05
1:100,000 w/v | 2 | 0.10
10 pnu/ml | 3 | 0.15
1 AU/ml | 4 | 0.20
1 BAU/ml | 5 | 0.30
 | 6 | 0.40
 | 7 | 0.50
Vial #2 | 8 | 0.05
1:10,000 w/v | 9 | 0.10
100 pnu/ml | 10 | 0.15
10 AU/ml | 11 | 0.20
10 BAU/ml | 12 | 0.30
 | 13 | 0.40
 | 14 | 0.50
Vial #3 | 15 | 0.05
1:1,000 w/v | 16 | 0.10
1,000 pnu/ml | 17 | 0.15
100 AU/ml | 18 | 0.20
100 BAU/ml | 19 | 0.30
 | 20 | 0.40
 | 21 | 0.50
Vial #4 | 22 | 0.05
1:100 w/v | 23 | 0.07
10,000 pnu/ml | 24 | 0.10
1,000 AU/ml | 25 | 0.15
1,000 BAU/ml | 26 | 0.20
 | 27 | 0.25
Maintenance Refill | 28 | 0.25
1:100 w/v | 29 | 0.25
10,000 pnu/ml | 30 | 0.25
1,000 AU/ml | 31 | 0.25
1,000 BAU/ml | 32 | 0.25
subsequent doses | 33 | 0.25

Preparation Instructions:

All dilutions may be made using sterile buffered diluent. The calculation may be based on the following ratio:

Volume desired x Concentration desired = Volume needed x Concentration available.

Example 1: If a 1:10 w/v extract is available and it is desired to use a 1:1,000 w/v extract substitute as follows:

Vd x Cd = Vn x Ca

10ml x 0.001 = Vn x 0.1

0.1 ml = Vn

Using a sterile technique, remove 0.10 ml of extract from the 1:10 vial and place it into a vial containing 9.90 ml of sterile diluent. The resulting ratio will be a 10 ml vial of 1:1,000 w/v.

Example 2: If a 10,000 pnu/ml extract is available and it is desired to use a 100 pnu/ml extract substitute as follows:

10ml x 100 = Vn x 10,000

0.1 ml = Vn

Using a sterile technique, remove 0.10 ml of extract from the 10,000 pnu/ml vial and place it into a vial containing 9.90 ml of sterile diluent. The resulting concentration will be a 10 ml vial of 100 pnu/ml.

Example 3: If a 10,000 AU/ml or BAU/ml extract is available and it is desired to use a 100 AU/ml or BAU/ml extract substitute as follows: Vd x Cd = Vn x Ca

10ml x 100 = Vn x 10,000

0.1 ml = Vn

Using a sterile technique, remove 0.10 ml of extract from the 10,000 AU/ml or BAU/ml vial and place it into a vial containing 9.90 ml of sterile diluent. The resulting concentration will be 10ml vial of 100 AU/ml or BAU/ml.

Intervals between doses: The optimal interval between doses of allergenic extract has not been definitely established. The amount of allergenic extract is increased at each injection by not more than 50%-100% of the previous amount and the next increment is governed by the response to the last injection. There are three generally accepted methods of pollen hyposensitizing therapy.

1. PRESEASONAL

Treatment starts each year 6 to 8 weeks before onset of seasonal symptoms. Maximal dose reached just before symptoms are expected. Injections discontinued during and following season until next year.

2. CO-SEASONAL

Patient is first treated during season with symptoms. Low initial doses are employed to prevent worsening of condition. This is followed by an intensive schedule of therapy (i.e. injections given 2 to 3 times per week). Fewer Allergists are resorting to this Co-seasonal therapy because of the availability of more effective, symptomatic medications that allow the patient to go through a season relatively symptom free.

3. PERENNIAL

Initially this is the same as pre seasonal. The allergen is administered twice weekly or weekly for about 20 injections to achieve the maximum tolerated dose. Then, maintenance therapy may be administered once a week or less frequently.

Duration of Treatment: The usual duration of treatment has not been established. A period of two or three years of injection therapy constitutes an average minimum course of treatment.

HOW SUPPLIED

Allergenic extracts are supplied with units listed as: Weight/volume (W/V), Protein Nitrogen Units (PNU/ml), Allergy Units (AU/ml) or Bioequivalent Allergy Units (BAU/ml).

Sizes:

Diagnostic Scratch: 5 ml dropper application vials

Diagnostic Intradermal: 5 ml or 10 ml vials.

Therapeutic Allergens: 5 ml, 10 ml, 50 ml multiple dose vials.

STORAGE

The expiration date of allergen extracts is listed on the container label. Store extracts upon arrival at 2° to 8°C and keep them in this range during office use.

WARRANTY: We warrant that this product was prepared and tested according to the standards of the FDA and is true to label. Because of biological differences in individuals and because allergenic extracts are manufactured to be potent and because we have no control over the conditions of use, we cannot and do not warrant either a good effect or against an ill effect following use.

REFERENCES

1 Jacobs, Robert L., Geoffrey W.Rake,Jr., et.al. Potentiated Anaphylaxis in Patients with Drug-induced Beta-adrenergic Blockade. J.Allergy & Clin. Immunol., 68(2): 125-127. August 1981.

2 Ishizaka,K.: Cellular Events in the IgE Antibody Response. Adv. in Immuno. 23:50-75, 1976.

3. Lockey, R.F., Bukantz, S.C., Allergen Immunotherapy. New York,NY: Marcel Dekker Inc., 1991.

4. Reid,M.J., Lockey,R.F., Turkeltaub,P.C., Platts-Mills,T.A.E., Survey of fatalities from skin testing and immunotherapy 1985-1989. Journal of Allergy Clin. Immunol. 92 (1): 6-15, July 1993.

5. Murray, A.B., Ferguson, A., Morrison, B., The frequency and severity of cat allergy vs dog allergy in atopic children. J. Allergy Clin. Immunolo: 72, 145-9, 1983.

6. Lockey, R.F., Bukantz, S.C., Allergen Immunotherapy. New York,NY: Marcel Dekker Inc., 1991.

ADDITIONAL INSTRUCTIONS DOSAGE FORM AND ROUTE OF ADMINISTRATION FOR USE OF ALLERGENIC EXTRACTS CONTAINING SHORT RAGWEED POLLEN

This is a supplement to Directions for Use and Suggested Dosage Schedule for Therapeutic Allergenic Extracts

INFORMATION RELATING TO ANTIGEN E

Antigen E Content in Concentrate: This product is compounded and diluted on a PNU or W/V basis. Extracts containing Short Ragweed Pollen also bear a labeled potency in terms of Antigen E content. The amount of Antigen E is expressed as units of Antigen E per mL of extract. Antigen E units are approximately equal to micrograms previously used to measure Antigen E concentration. Antigen E assay provides a measure of extract potency related to the E antigen in Short Ragweed, rather than only an expression of extract strength such as Protein Nitrogen Units (PNU) or Weight/Volume (W/V).

Example: Short Ragweed pollen extracted at 1:10 W/V usually assays within a range Of 70,000-100,000 PNU/mL and 100-400 AgE Units. (Analytical accuracy of the Antigen E assay is ±25%) Most treatment programs are W/V concentration of 1:100 to 1:20 or a PNU/mL concentrate of 20,000 to 40,000.

This would give a 70-100 AgE unit/mL concentration of Short Ragweed extract (Tall and Short Ragweed mix would be 1/2 this value).

New extraction lots of Short Ragweed will be labeled ac¬cording to W/V or PNU in addition to Antigen E content.

Antigen E Content in Mixtures: The Antigen E value applies only to the concentration of the Short Ragweed antigens contained in a concentrate. The Antigen E value does not express the total potency of the extract if Short Ragweed is mixed with another allergenic extract. Labeled Antigen content of extracts containing Short Ragweed at a concentration more dilute than a concentrate is determined by calculation. The formulae used for such calculations is given by:

V1 C1 = V2 C2

V1 = Volume of extract you wish to prepare

V2 = Volume of extract you need for dilution

C1 = Concentration (W/V, PNU/mL, units Antigen E/mL) you wish to prepare

C2 = Concentration of extract to be used

HOW SUPPLIED

Therapeutic allergens are available in l0mL and 50mL sterile multiple dose vials as individual allergens, stock mixture or mixture prescribed by the physician. Therapeutic allergens are standardized according to weight/volume.

Antigen E Short Ragweed and Tall and Short Ragweed mixture allergenic extracts are available in l0mL and 50mL dose vials at 1:10 and 40,000 PNU/mL aqueous or 1:20 and 20,000 PNU/mL with 50% glycerin.

SHORT RAGWEED AND MIXED RAGWEED

(Mixed Ragweed/equal parts of Short and Tall)

WARNING: This product is intended for use by or under the guidelines of physicians experienced and trained in the use allergenic extracts for hyposensitization and who are experienced in the emergency treatment of anaphylaxis.

PRECAUTIONS

The practitioner should have available the following: Epinephrine, tourniquet, parenteral fluids, bronchodilators, cardioactive drugs, as well as adequate oxygenation required for endotracheal intubation, emergency cricothyrotomy, or transtracheal catheterization if patient cannot be intubated.

In the event of systemic reactions characterized by one or more of the following: sneezing, mild to severe generalized urticaria, itching other than at the injection site, extensive or generalized edema, wheezing, asthma, dyspnea, cyanosis, tachycardia, lacrimation, marked perspiration, cough, hypotension, syncope, shock and upper airway obstruction, all of which may result in death, the following steps should taken: application of a tourniquet above the injection site and administration of 0.2 mL to 1.0 mL of Epinephrine Injection 1:1000 are recommended. Maximal recommended dose children under 2 years of age is 0.3 mL. Maximal recommended dose for children between 2 and 12 years of age is 0.5 mL. Following customary technique, the tourniquet is gradually released. The tourniquet should not be left in place without loosening for 90 seconds every 15 minutes. Volume expanders and vasopressor agents may be required to reverse hypotension. Inhaled bronchodialators and parenteral aminophylline may be required to reverse bronospasm.

Pregnancy Category C (Short Ragweed) - Animal reproduction studies have not been conducted with Short Ragweed. It is also not known whether Short Ragweed can cause fetal harm when administered to a pregnant woman or can affect reproduction capacity. Short Ragweed should be given to a pregnant woman only if clearly needed.

Pediatricis use: There is conflicting evidence as to the effectiveness of AgE extracts in children. Some studies have shown a decrease in clinical symptomatology.

GENERAL INFORMATION

1. Extract should be inspected visually for particulate matter and discoloration prior to administration whenever solution and product container permit.

2. In addition to the active ingredients - Short Ragweed pollen extract - this product contains 0.4% phenol as a preservative and as inactive ingredients - 0.5% NaCl and 0.275% NaHCO3.

3. All extracts are aseptically filled.

4. This product should be stored upon arrival at 2º C to 8º C as determined by stability data furnished by the FDA showing rapid drop in potency at temperatures above refrigerated temperatures for non-glycerinated products. 50% glycerin extracts maintain AgE stability much longer.

CLINICAL PHARMACOLOGY

Cumulative AgE dosage of less than 0.1 unit is not immunizing for most patients. This should not be interpreted as meaning that 0.1 unit is the maximum tolerated dosage. It has been shown that moderately sensitive patients may tolerate a dosage of ten to fifty times greater. For extremely sensitive patients who do not respond to treatment, the physician might consider immunotherapy with an alternative to the conventional aqueous allergenic extract.

INDICATIONS AND USAGE

This product is intended for use in the amelioration of symptoms associated with Short Ragweed allergy. If this is adjunctive therapy, beware of any regimen which might interfere with existing medications. Studies show that sufficient antigen dosage immunotherapy gives moderate or significant relief from Ragweed hayfever in adults.

Justification for use of this therapy can be derived from patient questionaires, daily diaries, respiratory function tests of airflow and lung volume and by immunological tests such as: leukocyte histamine release, measurement of allergenic specific IgE. lgG and IgA antibodies in serum and secretions, allergen provocation tests to skin, nose and lung.

CONTRAINDICATIONS

This product should not be used if the patient has a considerable identifiable risk such as asthma, cardiovascular disease, emphysema, diabetes or pregnancy, unless a specific diagnosis of type 1 allergy is made based on skin testing and the benefits of treatment are felt to outweigh the risks of an adverse reaction during testing or treatment.

ADVERSE REACTIONS

Defined as undesirable effects that are reasonably associated with product use, such as the following effects on various organ systems: erythema and pruritis of the skin, asthma effecting the lungs, tachycardia and angioedema of the heart and rhinitis of the nasal membranes.

Those reactions are mainly due to the interaction of allergen (antigen) with IgE specific antibodies, but other causes have not been excluded. For example, endotoxins, other types of reactions resuiting from prolonged immunotherapy, such as immune complex disease have been suggested as theoretical possibilities but not documented.

DOSAGE AND ADMINISTRATION

General Precautions: Sterile solutions, vials, syringes, etc. should be used and aseptic precautions observed in making dilutions. Dilution preparations should be tested for sterility. The usual precautions to be observed in administering extracts are necessary.

A sterile tuberculin syringe graduated in 0.1 mL units to measure each dose from the prescribed dilution should be used.

A treatment schedule is related directly to patient's sensitivity as determined first by skin testing and continuously by response to therapeutic doses. The potency of the intial injections should be adjusted to the patient's sensitivity. 1/10 of the lowest concentration producing positive ID skin test is usually safe.

Injections are administered subcutaneously, care to avoid injecting into blood vessels should be observed (Withdraw plunger gently. If blood appears, use a new injection site). A separate heat sterilized or sterile disposable syringe and needle should be used for each individual patient to prevent the transmission of homologous serum hepatitis and other infectious agents from one person to another.

Patient should always be observed for at least 30 minutes after any injection. If adverse reactions appear, the next therapeutic injection of extract should be reduced to the dose which does not elicit a reaction and subsequent doses increased more slowly.

A. 0.01 AgE/mL B. (0.005 AgE/mL) |  | 0.1 AgE/mL (0.05 AgE/mL) |  | 1.0 AgE/mL (0.5 AgE/mL) |  | 10 AgE/mL (5 AgE/mL) |  | 100 AgE/mL (50 AgE/mL)
Dose No. | Dose mL | Dose No. | Dose mL | Dose No. | Dose mL | Dose No. | Dose mL | Dose No. | Dose mL
1 | .03 | 7 | .03 | 13 | .03 | 19 | .03 | 25 | .03
2 | .05 | 8 | .05 | 14 | .05 | 20 | .05 | 26 | .05
3 | .08 | 9 | .08 | 15 | .08 | 21 | .08 | 27 | .08
4 | .12 | 10 | .12 | 16 | .12 | 22 | .12 | 28 | .12
5 | .20 | 11 | .20 | 17 | .20 | 23 | .20 | 29 | .20
6 | .30 | 12 | .30 | 18 | .30 | 24 | .30 | 30 | .30

Frequently dilutions of 1:100,000 W/V are prepared as the initial dilution or, in terms of Antigen E concentration, approximately 0.01 to 0.05 AgE units. For individuals which are hypersensitive, a more dilute extract is recommended, e.g. 1:1,000,000 W/V or 0.001 to 0.005 Antigen E/mL. A dose of 0.03 to 0.05 mL of this initial concentration is used initially and gradually increased in units of 0.03 mL (see above schedule) until a tolerance dose is reached or symptoms are controlled. Should a marked local reaction occur, the dosage should be lowered to a non-reactive dose before increasing once again.

Allergenic extracts become less potent with age. Should it therefore become necessary to treat a patient with a vial bearing a later expiration date, the initial dose of the extract should be lowered to a safe, non-reacting level.

Extremely sensitive patients may react to 0.01 units AgE or less on intradermal skin testing. For these patients a safe dose may be between 0.0004 and 0.0008 units of AgE requiring 100 fold dilution from dose one listed in the recommended table.

In transferring patients from unstandardized to standardized product, the physician should establish the potency relationship, perhaps by comparative skin testing at equal concentration, prior to injecting the first standardized dose.

1.Lowell. F.C., et. al., "Journal of Allergy" 34, 165 (1963)

2.Ibid. "New Eng. Journal of Medicine" 273, 675 (1965)

3.Lichtenstein, L.M. et. al., "American Journal of Medicine" 44, 514 (1968)

4.Lichtenstein, L.M. et. al., "Journal of Allergy and Clinical Immunology" 61, 370 (1978)

5.Van Metre, T.E. and Lichtenstein, L.M. et. al., "Journal of Allergy and Clinical Immunology" 60, 181 (1982)

6.Lessof and Lippincott, "Immunologic Apsects of Allergy" 81, 300 (1981)